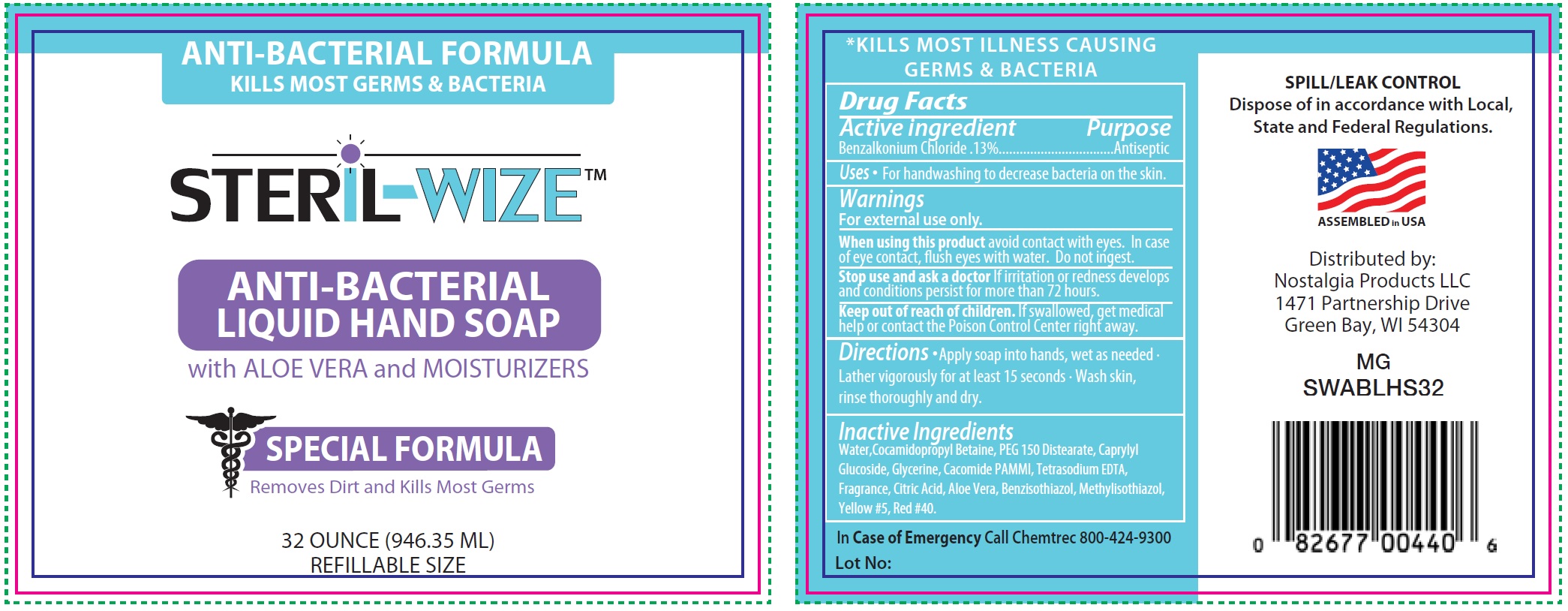 DRUG LABEL: Steril Wize Anti Bacterial Liquid Hand
NDC: 77051-002 | Form: SOAP
Manufacturer: Nostalgia Products LLC
Category: otc | Type: HUMAN OTC DRUG LABEL
Date: 20200706

ACTIVE INGREDIENTS: BENZALKONIUM CHLORIDE 1.3 mg/1 mL
INACTIVE INGREDIENTS: WATER; COCAMIDOPROPYL BETAINE; PEG-150 DISTEARATE; CAPRYLYL GLUCOSIDE; GLYCERIN; EDETATE SODIUM; CITRIC ACID MONOHYDRATE; ALOE VERA LEAF; FD&C YELLOW NO. 5; FD&C RED NO. 40

Steril-Wize Anti-Bacterial Liquid Hand Soap

Active ingredient

Benzalkonium Chloride .13%

Purpose

Antiseptic

Uses

- For handwashing to decrease bacteria on the skin.

Warnings

For external use only.

When using this product

avoid contact with eyes. In case of eye contact, flush eyes with water. Do not ingest.

Stop use and ask a doctor

If irritation or redness develops and conditions persist for more than 72 hours.

Keep out of reach of children.

If swallowed, get medical help or contact the Poison Control Center right away.

Directions

- Apply soap into hands, wet as needed
- Lather vigorously for at least 15 seconds · Wash skin, rinse thoroughly and dry.

Inactive Ingredients

Water,Cocamidopropyl Betaine, PEG 150 Distearate, Caprylyl Glucoside, Glycerine, Cacomide PAMMI, Tetrasodium EDTA, Fragrance, Citric Acid, Aloe Vera, Benzisothiazol, Methylisothiazol, Yellow #5, Red #40.